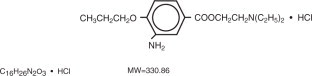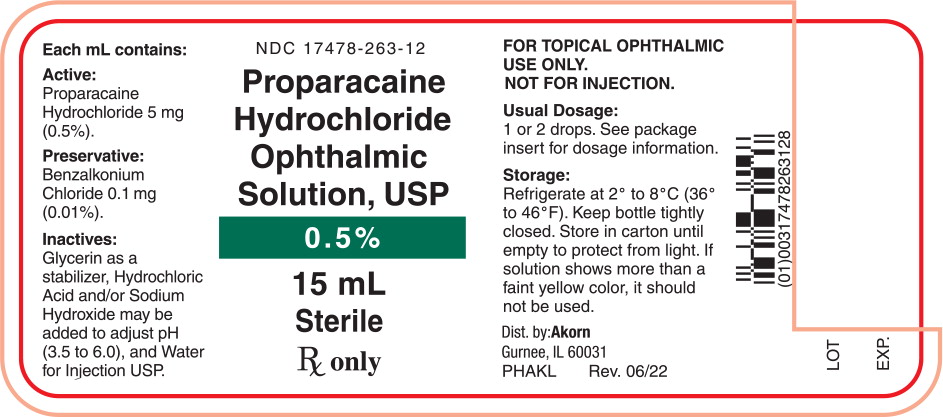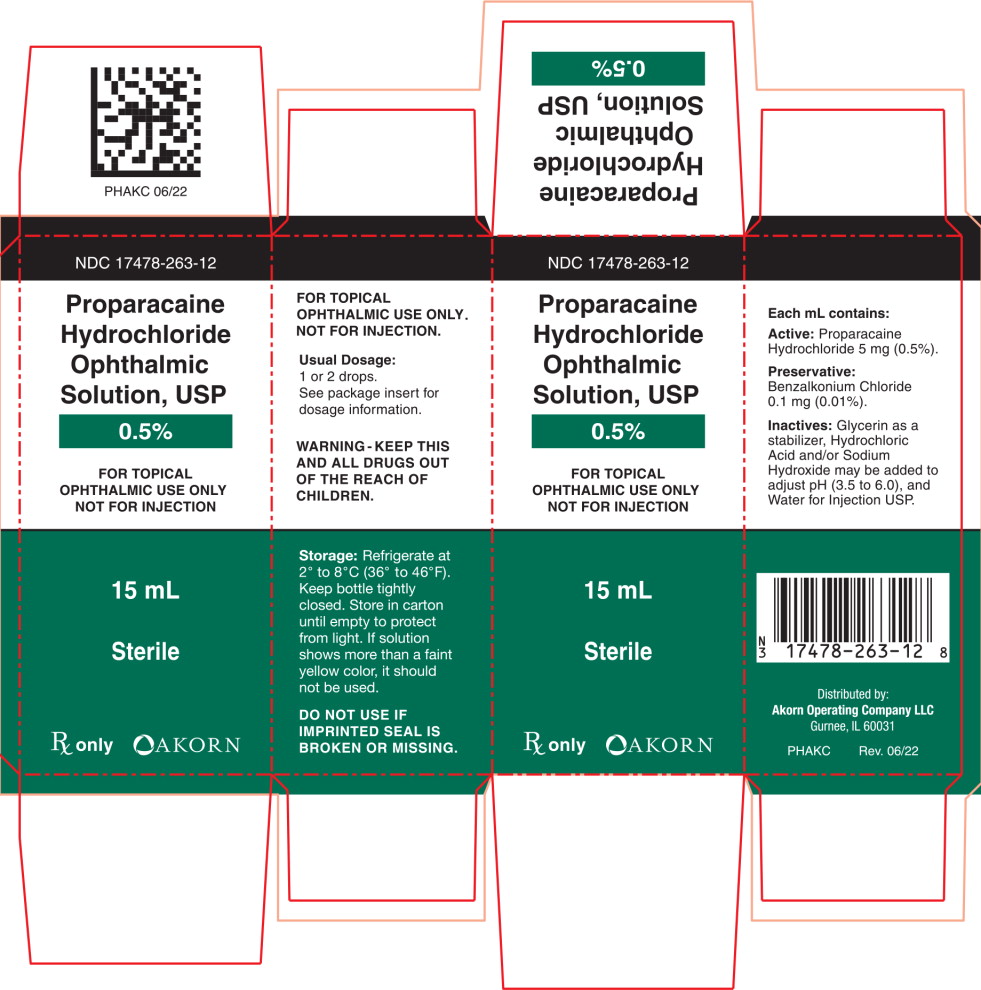 DRUG LABEL: Proparacaine Hydrochloride
NDC: 17478-263 | Form: SOLUTION/ DROPS
Manufacturer: Akorn
Category: prescription | Type: HUMAN PRESCRIPTION DRUG LABEL
Date: 20220909

ACTIVE INGREDIENTS: Proparacaine Hydrochloride 5 mg/1 mL
INACTIVE INGREDIENTS: Glycerin; Hydrochloric Acid; Sodium Hydroxide; Water; Benzalkonium Chloride

Proparacaine Hydrochloride Ophthalmic Solution USP, 0.5% Sterile

Sterile

Rx only

DESCRIPTION

Proparacaine Hydrochloride Ophthalmic Solution USP, 0.5% is a local anesthetic for ophthalmic instillation. Each mL of sterile, aqueous solution contains: Active: Proparacaine Hydrochloride 5 mg (0.5%). Preservative: Benzalkonium Chloride 0.1 mg (0.01%). Inactives: Glycerin as a stabilizer, Hydrochloric Acid and/or Sodium Hydroxide may be added to adjust pH (3.5 to 6.0), and Water for Injection USP.

Proparacaine hydrochloride is designed chemically as 2-(Diethylamino)ethyl 3-amino-4-propoxybenzoate monohydrochloride. The active ingredient is represented by the structural formula:

CLINICAL PHARMACOLOGY

Proparacaine Hydrochloride Ophthalmic Solution is a rapid acting local anesthetic suitable for ophthalmic use. With a single drop, the onset of anesthesia begins within 30 seconds and persists for 15 minutes or longer.

The main site of anesthetic action is the nerve cell membrane where proparacaine interferes with the large transient increase in the membrane permeability to sodium ions that is normally produced by a slight depolarization of the membrane. As the anesthetic action progressively develops in a nerve, the threshold for electrical stimulation gradually increases and the safety factor for conduction decreases; when this action is sufficiently well developed, block of conduction is produced.

The exact mechanism whereby proparacaine and other local anesthetics influence the permeability of the cell membrane is unknown; however, several studies indicate that local anesthetics may limit sodium ion permeability by closing the pores through which the ions migrate in the lipid layer of the nerve cell membrane. This limitation prevents the fundamental change necessary for the generation of the action potential.

INDICATIONS AND USAGE

Proparacaine Hydrochloride Ophthalmic Solution is indicated for topical anesthesia in ophthalmic practice. Representative ophthalmic procedures in which the preparation provides good local anesthesia include measurement of intraocular pressure (tonometry), removal of foreign bodies and sutures from the cornea, conjunctival scraping in diagnosis and gonioscopic examination; it is also indicated for use as a topical anesthetic prior to surgical operations such as cataract extraction.

CONTRAINDICATIONS

This preparation is contraindicated in patients with known hypersensitivity to any component of the solution.

WARNINGS

NOT FOR INJECTION. FOR TOPICAL OPHTHALMIC USE ONLY.

Prolonged use of a topical ocular anesthetic may produce permanent corneal opacification with accompanying loss of vision.

PRECAUTIONS

General

Proparacaine should be used cautiously and sparingly in patients with known allergies, cardiac disease, or hyperthyroidism. The long-term toxicity of proparacaine is unknown; prolonged use may possibly delay wound healing. Although exceedingly rare with ophthalmic application of local anesthetics, it should be borne in mind that systemic toxicity (manifested by central nervous system stimulation followed by depression) may occur.

Protection of the eye from irritating chemicals, foreign bodies and rubbing during the period of anesthesia is very important. Tonometers soaked in sterilizing or detergent solutions should be thoroughly rinsed with sterile distilled water prior to use. Patients should be advised to avoid touching the eye until the anesthesia has worn off. Do not touch dropper tip to any surface as this may contaminate the solution.

Carcinogenesis, Mutagenesis, Impairment of Fertility

Long-term studies in animals have not been performed to evaluate carcinogenic potential, mutagenicity, or possible impairment of fertility in males or females.

Pregnancy

Teratogenic Effects

Category C

Animal reproduction studies have not been conducted with Proparacaine Hydrochloride Ophthalmic Solution. It is also not known whether proparacaine hydrochloride can cause fetal harm when administered to a pregnant woman or can affect reproduction capacity. Proparacaine hydrochloride should be administered to a pregnant woman only if clearly needed.

Nursing Mothers

It is not known whether this drug is excreted in human milk. Because many drugs are excreted in human milk, caution should be exercised when proparacaine hydrochloride is administered to a nursing woman.

Pediatric Use

Controlled clinical studies have not been performed with Proparacaine Hydrochloride Ophthalmic Solution to establish safety and effectiveness in pediatric patients; however, the literature cites the use of proparacaine hydrochloride as a topical ophthalmic anesthetic agent in pediatric patients.

ADVERSE REACTIONS

Pupillary dilatation or cycloplegic effects have rarely been observed with proparacaine hydrochloride. The drug appears to be safe for use in patients sensitive to other local anesthetics, but local or systemic sensitivity occasionally occurs. Instillation of proparacaine in the eye at recommended concentration and dosage usually produces little or no initial irritation, stinging, burning, conjunctival redness, lacrimation or increased winking. However, some local irritation and stinging may occur several hours after the instillation.

Rarely, a severe, immediate-type, apparently hyperallergic corneal reaction may occur which includes acute, intense and diffuse epithelial keratitis; a gray, ground-glass appearance; sloughing of large areas of necrotic epithelium; corneal filaments and, sometimes, iritis with descemetitis.

Allergic contact dermatitis with drying and fissuring of the fingertips has been reported.

Softening and erosion of the corneal epithelium and conjunctival congestion and hemorrhage have been reported.

DOSAGE AND ADMINISTRATION

Deep anesthesia as in cataract extraction:

Instill 1 drop to the eye every 5 to 10 minutes for 5 to 7 doses.

Removal of sutures:

Instill 1 or 2 drops to the eye 2 or 3 minutes before removal of stitches.

Removal of foreign bodies:

Instill 1 or 2 drops to the eye prior to operating.

Tonometry:

Instill 1 or 2 drops to the eye immediately before measurement.

HOW SUPPLIED

Proparacaine Hydrochloride Ophthalmic Solution USP, 0.5% is supplied as a sterile solution in 15 mL plastic dropper bottles — NDC 17478-263-12

STORAGE

Refrigerate at 2° to 8°C (36° to 46°F). Keep bottle tightly closed. Store in carton until empty to protect from light. If solution shows more than a faint yellow color, it should not be used.

WARNING — KEEP THIS AND ALL DRUGS OUT OF THE REACH OF CHILDREN.

Akorn
Distributed by:
Akorn Operating Company LLC
Gurnee, IL 60031

NJPH00N
Rev. 06/22

Principal Display Panel Text for Container Label:

NDC 17478-263-12

Proparacaine

Hydrochloride

Ophthalmic

Solution, USP

0.5%

15 mL

Rx only

Principal Display Panel Text for Carton Label:

NDC 17478-263-12

Proparacaine

Hydrochloride

Ophthalmic

Solution, USP

0.5%

FOR TOPICAL

OPHTHALMIC USE ONLY

NOT FOR INJECTION

15 mL

Sterile

Rx only Akorn Logo